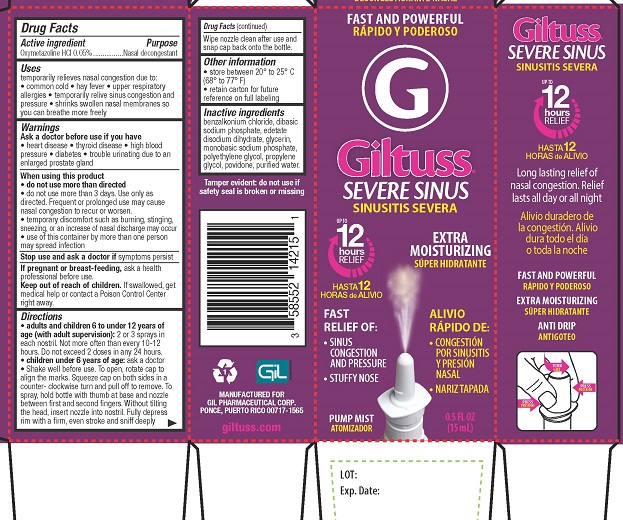 DRUG LABEL: Giltuss Severe Sinus
NDC: 58552-142 | Form: SPRAY
Manufacturer: Gil Pharmaceutical Corp
Category: otc | Type: HUMAN OTC DRUG LABEL
Date: 20251009

ACTIVE INGREDIENTS: OXYMETAZOLINE HYDROCHLORIDE 0.05 g/100 mL
INACTIVE INGREDIENTS: GLYCERIN; BENZALKONIUM CHLORIDE; EDETATE DISODIUM; POLYETHYLENE GLYCOL, UNSPECIFIED; POVIDONE, UNSPECIFIED; PROPYLENE GLYCOL; WATER; SODIUM PHOSPHATE, MONOBASIC; SODIUM PHOSPHATE, DIBASIC

Giltuss Severe Sinus Nasal Spray

Drug Facts

Active ingredient

Oxymetazoline HCl 0.05%

Purpose

Nasal decongestant

Uses
temporarily relieves nasal congestion due to:

- common cold
- hay fever
- upper respiratory allergies
- temporarily relive sinus congestion and pressure
- shrinks swollen nasal membrances so you can breathe more freely

Warnings

Ask a doctor before use if you have

- heart disease
- thyroid disease
- high blood pressure
- diabetes
- trouble urinating due to an enlarged prostate gland

When using this product

- do not use more than directed
- do not use for more than 3 days. Use only as directed. Frequent or prolonged use may cause nasal congestion to recur or worsen.
- temporary discomfort such as burning, stinging, sneezing, or an increase in nasal discharge may occur
- use of this container by more than one person may spread infection

Stop use and ask a doctor ifsymptoms persist

PREGNANCY OR BREAST FEEDING

If pregnant or breast-feeding,ask a health professional before use.

Keep out of reach of children.If swallowed, get medical help or contact a Poison Control Center right away.

Directions

- adults and children 6 to under 12 years of age (with adult supervision):2 or 3 sprays in each nostrill. Not more often than every 10 to 12 hours. Do not exceed 2 doses in any 24-hour period.
- children under 6 years of age:ask a doctor.
- Shake well before use. To open, rotate cap to align the marks. Squeeze cap on both sides in a counter-clockwise turn and pull off to remove. To spray, hold bottle with thumb at base and nozzle between first and second fingers. Without tilting the head, insert nozzle into nostril. Fully depress with a firm, even stroke and sniff deeply. Wipe nozzle clean after use and snap cap back onto the bottle.

Other information

- store between 20° to 25°C (68° to 77° F)
- retain carton for future reference on full labeling

Inactive Ingredients

benzalkonium chloride, dibasic sodium phosphate, edetate disodium dihydrate, glycerin, monobasic sodium phosphate, polyethylene glycol, propylene glycol, povidone, purified water.

Tamper evident: do not use if safety seal is broken or missing

MANUFACTURED FOR GIL PHARMACEUTICAL CORP.

PONCE, PUERTO RICO 00717-1565

giltuss.com

PACKAGE LABEL

FAST AND POWERFUL

Giltuss®

SEVERE SINUS

UP TO 12 HOURS RELIEF

EXTRA MOISTURIZING

FAST RELIEF OF:

- SINUS CONGESTION AND PRESSURE
- STUFFY NOSE

PUMP MIST

0.5 FL OZ (15 mL)